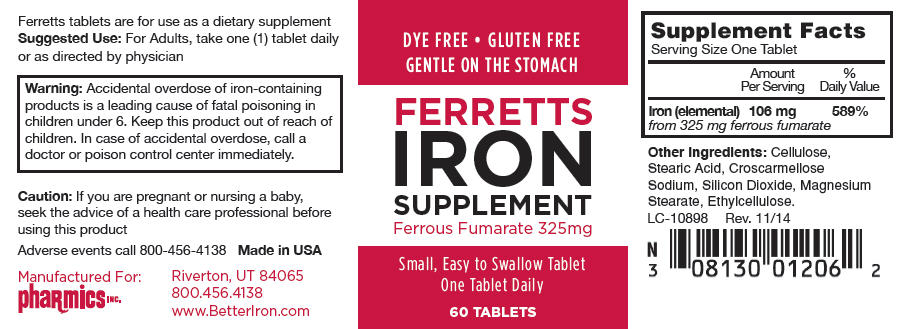 DRUG LABEL: Ferretts
NDC: 0813-0012 | Form: TABLET, FILM COATED
Manufacturer: Pharmics, Inc.
Category: other | Type: DIETARY SUPPLEMENT
Date: 20150108

ACTIVE INGREDIENTS: Ferrous Fumarate 325 mg/1 1
INACTIVE INGREDIENTS: Cellulose, Microcrystalline; Stearic Acid; CROSCARMELLOSE SODIUM; Silicon Dioxide; Magnesium Stearate; Ethylcelluloses

Ferretts
Iron Supplement

STATEMENT OF IDENTITY

Supplement Facts

Serving Size One Tablet

Amount Per Serving

% Daily Value

Iron (elemental)

106 mg

589%

from 325 mg ferrous fumarate

Other Ingredients: Cellulose, Stearic Acid, Croscarmellose Sodium, Silicon Dioxide, Magnesium Stearate, Ethylcellulose.

HEALTH CLAIM

Ferretts tablets are for use as a dietary supplement

Suggested Use

For Adults, take one (1) tablet daily or as directed by physician

WARNINGS

Warning: Accidental overdose of iron-containing products is a leading cause of fatal poisoning in children under 6. Keep this product out of reach of children. In case of accidental overdose, call a doctor or poison control center immediately.

Caution

If you are pregnant or nursing a baby, seek the advice of a health care professional before using this product

HEALTH CLAIM

Adverse events call 800-456-4138 Made in USA

Manufactured For:
pha℞mics INC.
Riverton, UT 84065
800.456.4138
www.BetterIron.com

LC-10898
Rev. 11/14

PRINCIPAL DISPLAY PANEL - 60 Tablet Bottle Label

DYE FREE • GLUTEN FREE
GENTLE ON THE STOMACH

FERRETTS
IRON
SUPPLEMENT
Ferrous Fumarate 325mg

Small, Easy to Swallow Tablet
One Tablet Daily

60 TABLETS